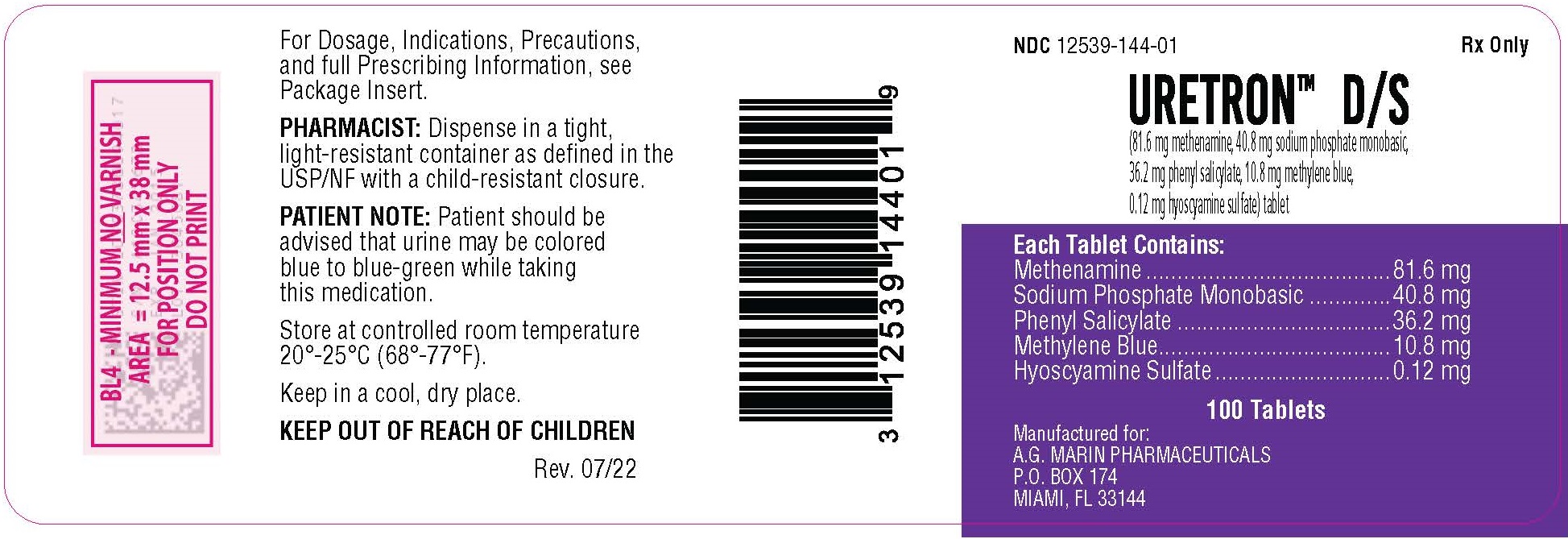 DRUG LABEL: Uretron D/S
NDC: 12539-144 | Form: TABLET
Manufacturer: DORAL PHARMAMEDICS INC dba A.G. Marin Pharmaceuticals
Category: prescription | Type: HUMAN PRESCRIPTION DRUG LABEL
Date: 20251218

ACTIVE INGREDIENTS: SODIUM PHOSPHATE, MONOBASIC, MONOHYDRATE 40.8 mg/1 1; PHENYL SALICYLATE 36.2 mg/1 1; HYOSCYAMINE SULFATE 0.12 mg/1 1; METHYLENE BLUE 10.8 mg/1 1; METHENAMINE 81.6 mg/1 1
INACTIVE INGREDIENTS: FD&C BLUE NO. 1 ALUMINUM LAKE; CROSPOVIDONE; ANHYDROUS DIBASIC CALCIUM PHOSPHATE; MAGNESIUM STEARATE; CELLULOSE, MICROCRYSTALLINE; POLYETHYLENE GLYCOL; POLYVINYL ALCOHOL; STEARIC ACID; TALC; TITANIUM DIOXIDE

Uretron D/S

Rx Only

100 Tablets

DESCRIPTION

Uretron™D/S tablets for oral administration

Each tablet contains:
Methenamine | 81.6 mg
Sodium Phosphate Monobasic | 40.8 mg
Phenyl Salicylate | 36.2 mg
Methylene Blue | 10.8 mg
Hyoscyamine Sulfate | 0.12 mg

HYOSCYAMINE SULFATE. [620-61-1][3(S)-endo]-α-(Hydroxymethyl)-benzeneacetic acid 8-methyl-8-azabicyclo[3.2.1]oct-3-yl ester sulfate(2:1)(salt); 1αH,5αH-tropan-3α-ol(-)-tropate(ester) sulfate(2:1)(salt);3α-tropanyl S-(-)-tropate; l-tropic acid ester with tropine; l-tropine tropate. C34H48N2O10S. Hyoscyamine Sulfate is an alkaloid of belladonna. Exists as a white crystalline powder. Its solutions are alkaline to litmus. Affected by light, it is slightly soluble in water; freely soluble in alcohol; sparingly soluble in ether.

METHENAMINE. [100-97-0] 1,3,5,7-Tetraazatricyclo [3.3.1.-1^3,7] decane; hexamethylenetetramine; HMT; HMTA; hexamine; 1,3,5,7-tetraazaadamantane hexamethylenemine; Uritone; Urotropin. C6H12N4; mol wt 140.19; C 51.40%, H 8.63%, N 39.96%. Methenamine (hexamethylenetetramine) exists as colorless, lustrous crystals or white crystalline powder. Its solutions are alkaline to litmus. Freely soluble in water, soluble in alcohol and in chloroform.

METHYLENE BLUE. [61-73-4] 3,7-Bis(dimethylamino) phenothiazin-5-ium chloride; C.I. Basic Blue 9; methylthioninium chloride; tetramethylthionine chloride; 3,7-bis(dimethylamino) phenazathionium chloride. C16H18ClN3S; mol wt 319.85, C 60.08%, H 5.67%, Cl 11.08%, N 13.14%, S 10.03%. Methylene Blue (Methylthionine chloride) exists as dark green crystals. It is soluble in water and in chloroform; sparingly soluble in alcohol.

PHENYL SALICYLATE. [118-55-8] 2-Hydroxybenzoic acid phenyl ester; Salol. C13H10O3; mol wt 214.22, C 72.89%, H 4.71%, O 22.41%. Made by the action of phosphorus oxy-chloride on a mixture of phenol and salicylic acid. Phenyl Salicylate exists as white crystals with a melting point of 41°-43° C. It is very slightly soluble in water and freely soluble in alcohol.

SODIUM PHOSPHATE MONOBASIC. [7558-80-7] Phosphoric acid sodium salt (1:1); Sodium biphosphate; sodium dihydrogen phosphate; acid sodium phosphate; monosodium orthophosphate; primary sodium phosphate; H2NaO4P; mol wt 119.98, H 1.68%, Na 19.16%, O 53.34%, P 25.82%. Monohydrate, white, odorless slightly deliquesce crystals or granules. At 100° C loses all its water; when ignited it converts to metaphosphate. It is freely soluble in water and practically insoluble in alcohol. The aqueous solution is acid. pH of 0.1 molar aqueous solution at 25° C: 4.5.

Uretron D/Stablets contain inactive ingredients: Crospovidone, Dicalcium Phosphate, FD&C Blue #1 Aluminum Lake, Magnesium Stearate, Microcrystalline Cellulose, Polyethylene Glycol, Polyvinyl Alcohol, Stearic Acid, Talc, and Titanium Dioxide.

CLINICAL PHARMACOLOGY

HYOSCYAMINE SULFATE is a parasympatholytic which relaxes smooth muscles and thus produces an antispasmodic effect. It is well absorbed from the gastrointestinal tract and is rapidly distributed throughout the body tissues. Most is excreted in the urine within 12 hours, 13% to 50% being unchanged. Its biotransformation is hepatic. Its protein binding is moderate.

METHENAMINE degrades in an acidic urine environment releasing formaldehyde which provides bactericidal or bacteriostatic action. It is well absorbed from the gastrointestinal tract. 70%-90% reaches the urine unchanged at which point it is hydrolyzed if the urine is acidic. Within 24 hours it is almost completely (90%) excreted; of this at a pH of 5, approximately 20% is formaldehyde. Protein binding - some formaldehyde is bound to substances in the urine and surrounding tissues. Methenamine is freely distributed to body tissue and fluids but is not clinically significant as it does not hydrolyze at pH greater than 6.8.

METHYLENE BLUE possesses weak antiseptic properties. It is well absorbed by the gastrointestinal tract and rapidly reduced to leukomethylene blue which is stabilizied in some combination form in the urine. 75% is excreted unchanged.

PHENYL SALICYLATE releases salicylate, a mild analgesic for pain.

SODIUM PHOSPHATE MONOBASIC an acidifier, helps to maintain an acid pH in the urine necessary for the degradation of methenamine.

INDICATIONS AND USAGE

Uretron D/Stablets are indicated for the treatment of symptoms of irritative voiding. Indicated for the relief of local symptoms, such as inflammation, hypermotility, and pain, which accompany lower urinary tract infections. Indicated for the relief of urinary tract symptoms caused by diagnostic procedures.

CONTRAINDICATIONS

Hypersensitivity to any of the ingredients is possible.

Risk benefits should be carefully considered when the following medical problems exist: cardiac disease (especially cardiac arrhythmias, congestive heart failure, coronary heart disease, and mitral stenosis); gastrointestinal tract obstructive disease; glaucoma; myasthenia gravis, acute urinary retention may be precipitated in obstructive uropathy (such as bladder neck obstruction due to prostatic hypertrophy).

WARNINGS

Do not exceed recommended dosage. If rapid pulse, dizziness or blurring of vision occurs discontinue use immediately.

PRECAUTIONS

Cross sensitivity and/or related problems

Patients intolerant of belladonna alkaloids or salicylates may be intolerant of this medication also. Delay in gastric emptying could complicate the management of gastric ulcers.

Pregnancy/Reproduction

FDA Pregnancy Category C

Hyoscyamine and methenamine cross the placenta. Studies concerning the effect of hyoscyamine and methenamine on pregnancy and reproduction have not been done in animals or humans. Thus it is not known whether Uretron D/Stablets cause fetal harm when administered to a pregnant woman or can affect reproduction capacity. Uretron D/Sshould be given to a pregnant woman only if clearly needed.

Breast feeding

Problems in humans have not been documented; however, methenamine and traces of hyoscyamine are excreted in breast milk. Accordingly, Uretron D/Stablets should be given to a nursing mother with caution and only if clearly needed.

Prolonged use

There have been no studies to establish the safety of prolonged use in humans. No known long-term animal studies have been performed to valuate carcinogenic potential.

Pediatric

Infants and young children are especially susceptible to the toxic effect of the belladonna alkaloids.

Geriatric Use

Use with caution in elderly patients as they may respond to usual doses of hyoscyamine with excitement, agitation, drowsiness or confusion.

ADVERSE REACTIONS

Cardiovascular: rapid heartbeat, flushing

Central Nervous System: blurred vision, dizziness, drowsiness

Genitourinary: difficult micturition, acute urinary retention

Gastrointestinal: dry mouth, nausea and vomiting

Respiratory: shortness of breath or trouble breathing

Serious allergic reactions to this drug are rare. Seek immediate medical attention if you notice symptoms of a serious allergic reaction, including itching, rash, severe dizziness, swelling or trouble breathing.

This medication can cause urine and sometimes stools to turn blue to blue-green. This effect is harmless and will subside after medication is stopped.

Call your doctor or physician for medical advice about side effects. To report SUSPECTED ADVERSE REACTIONS, contact A.G. Marin Pharmaceuticals at 305-593-5333 or FDA at 1-800-FDA-1088, www.fda.gov/medwatch.

Drug interactions

As a result of hyoscyamine's effects on gastrointestinal motility and gastric emptying, absorption of other oral medications may be decreased during concurrent use with this combination medication.
Methylene blue inhibits a range of CYP isozymes in vitro, including 1A2, 2B6, 2C8, 2C9, 2C19, 2D6 and 3A4/5. This interaction could be more pronounced with narrow therapeutic index drugs that are metabolized by one of these enzymes (e.g., digoxin, warfarin, phenytoin, alfentanil, cyclosporine, dihydroergotamine, ergotamine, fentanyl, pimozide, quinidine, sirolimus and tacrolimus). However, the clinical relevance of these in vitro interactions is unknown.
Urinary alkalizers and thiazide diuretics:May cause the urine to become alkaline reducing the effectiveness of methenamine by inhibiting its conversion to formaldehyde.
Antimuscarinics: Concurrent use may intensify antimuscarinic effects of hyoscyamine because of secondary antimuscarinic activities of these medications.
Antacids/antidiarrheals:Concurrent use may reduce absorption of hyoscyamine resulting in decreased therapeutic effectiveness. Concurrent use with antacids may cause urine to become alkaline reducing the effectiveness of methenamine by inhibiting its conversion to formaldehyde. Doses of these medications should be spaced 1 hour apart from doses of hyoscyamine.
Antimyasthenics:Concurrent use with hyoscyamine may further reduce intestinal motility, therefore, caution is recommended.
Ketoconazole and hyoscyamine may cause increased gastrointestinal pH. Concurrent administration with hyoscyamine may result in marked reduction in the absorption of ketoconazole. Patients should be advised to take this combination at least 2 hours
after ketoconazole.
Monoamine oxidase (MAO) inhibitors:Concurrent use with hyoscyamine may intensify antimuscarinic side effects.
Opioid (narcotic) analgesics may result in increased risk of severe constipation.
Sulfonamides:These drugs may precipitate with formaldehyde in the urine increasing the danger of crystalluria.
Patients should be advised that the urine and/or stools may become blue to blue-green as a result of the excretion of methylene blue.

DRUG ABUSE AND DEPENDENCE

A dependence on the use of Uretron D/S tablets has not been reported and due to the nature of its ingredients, abuse of Uretron D/S tablets is not expected.

OVERDOSAGE

Emesis or gastric lavage. Slow intravenous administration of physostigmine in doses of 1 to 4 mg (0.5 to 1 mg in children), repeated as needed in one to two hours to reverse severe antimuscarinic symptoms.

Administration of small doses of diazepam to control excitement and seizures. Artificial respiration with oxygen if needed for respiratory depression. Adequate hydration. Symptomatic treatment as necessary.

If overdose is suspected, contact your local poison center or emergency room immediately. US residents can contact the US National Poison Hotline at 1-800-222-1222.

DOSAGE AND ADMINISTRATION

Adults - One tablet orally 4 times per day followed by liberal fluid intake.

Older Children -Dosage must be individualized by physician. Not recommended for use in children six years of age or younger.

HOW SUPPLIED

Uretron D/Stablets are blue tablets imprinted with "SAT" on one side and "902" on opposite side.

NDC12539-144-01, Bottle of 100 Tablets.

STORAGE

Dispense in a tight, light-resistant container as defined in the USP/NF with a child resistant closure.

Store at controlled room temperature 20°-25°C (68°-77°F).

Keep in a cool, dry place. Keep container tightly closed.

Keep this and all drugs out of reach of children.

Rx Only

Manufactured for:
A.G. MARIN PHARMACEUTICALS
P.O. BOX 174
MIAMI, FL 33144